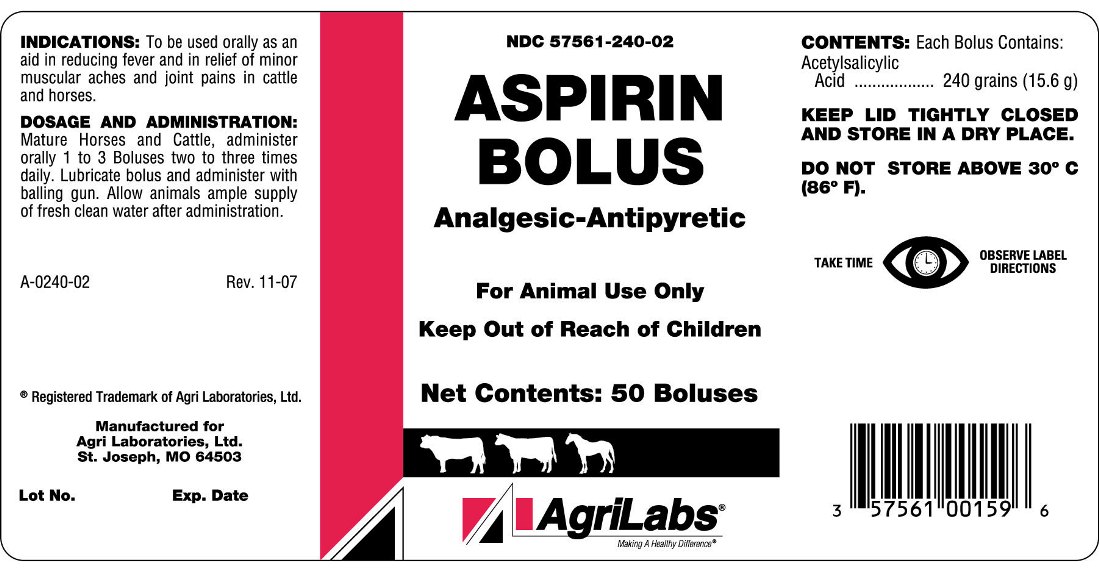 DRUG LABEL: ASPIRIN BOLUS
NDC: 57561-240 | Form: TABLET
Manufacturer: Agri Laboratories, Ltd.
Category: animal | Type: OTC ANIMAL DRUG LABEL
Date: 20140716

ACTIVE INGREDIENTS: ASPIRIN 15.6 g/1 1

ASPIRIN BOLUS

INDICATIONS AND USAGE

Analgesic-Antipyretic

For Animal Use Only

Keep Out of Reach of Children

INDICATIONS

To be used orally as an aid in reducing fever and in relief of minor muscular aches and joint pains in cattle and horses.

DOSAGE AND ADMINISTRATION

Mature Horses and Cattle, administer orally 1 to 3 Boluses two to three times daily. Lubricate bolus and administer with balling gun. Allow animals ample supply of fresh clean water after administration.

CONTENTS

Each Bolus Contains:

Acetylsalicylic Acid ................................. 240 grains (15.6 g)

STORAGE AND HANDLING

KEEP LID TIGHTLY CLOSED AND STORE IN A DRY PLACE.

DO NOT STORE ABOVE 30oC (86oF)

TAKE TIME OBSERVE LABEL DIRECTIONS